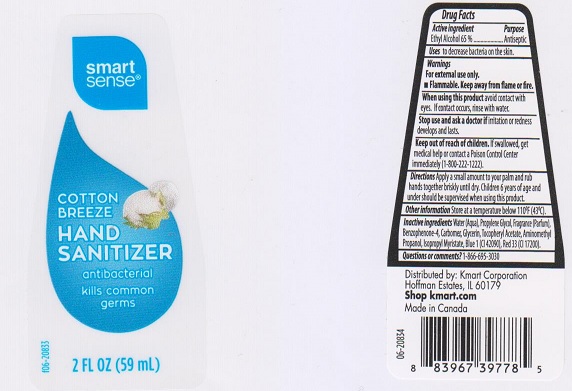 DRUG LABEL: Smart Sense Hand Sanitizer Cotton Breeze
NDC: 49738-408 | Form: LIQUID
Manufacturer: Kmart Corporation
Category: otc | Type: HUMAN OTC DRUG LABEL
Date: 20161004

ACTIVE INGREDIENTS: ALCOHOL 650 mg/1 mL
INACTIVE INGREDIENTS: WATER; PROPYLENE GLYCOL; SULISOBENZONE; CARBOMER 934; GLYCERIN; .ALPHA.-TOCOPHEROL ACETATE, DL-; AMINOMETHYLPROPANOL; ISOPROPYL MYRISTATE; FD&C BLUE NO. 1; D&C RED NO. 33

Drug Facts

Active ingredient

Ethyl Alcohol 65%

Purpose

Antiseptic

Uses

to decrease bacteria on the skin.

Warnings

For external use only.

- Flammable. Keep away from flame or fire.

When using this product

avoid contact with eyes. If contact occurs, rinse with water.

Stop use and ask a doctor if

irritation or redness develops and lasts.

Keep out of reach of children.

If swallowed, get medical help or contact a Poison Control Center immediately (1-800-222-1222).

Directions

Apply a small amount to your palm and rub hands together briskly until dry. Children 6 years of age and under should be supervised when using this product.

Other information

Store at a temperature below 110°F (43°C).

Inactive ingredients

Water (Aqua), Propylene Glycol, Fragrance (Parfum), Benzophenone-4, Carbomer, Glycerin, Tocopheryl Acetate, Aminomethyl Propanol, Isopropyl Myristate, Blue 1 (CI 42090), Red 33 (CI 17200).

Questions or comments?

1-866-695-3030